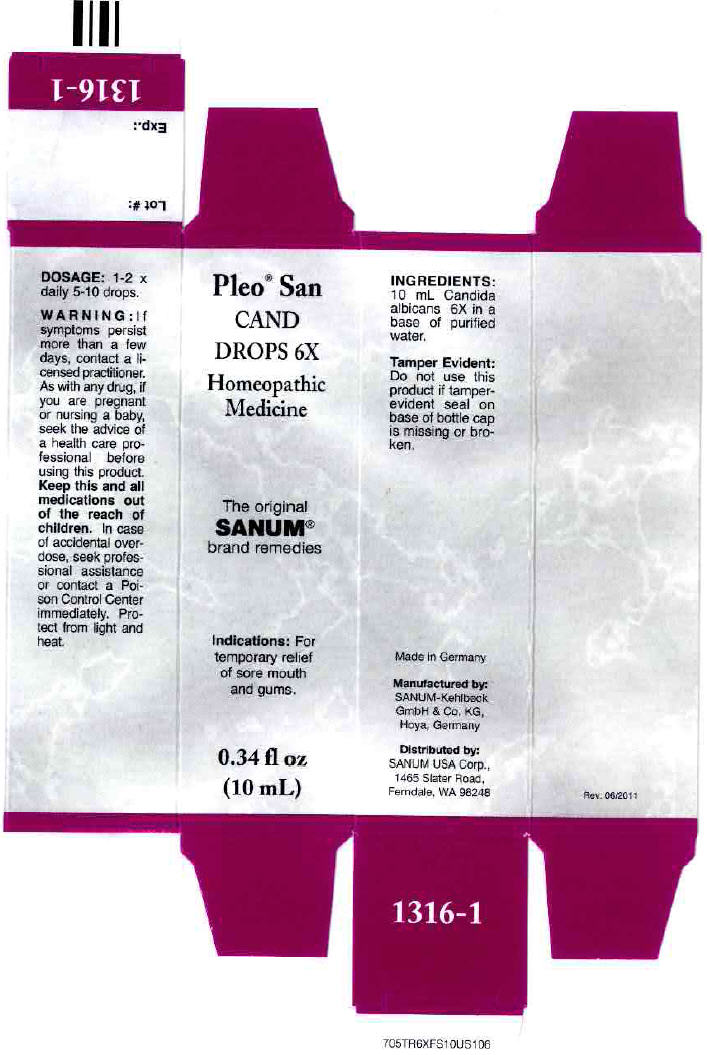 DRUG LABEL: Pleo San Cand
NDC: 60681-1316 | Form: SOLUTION/ DROPS
Manufacturer: Sanum-Kehlbeck GmbH & Co. KG
Category: homeopathic | Type: HUMAN OTC DRUG LABEL
Date: 20120307

ACTIVE INGREDIENTS: candida albicans 6 [hp_X]/10 mL
INACTIVE INGREDIENTS: water

Pleo™ San
CAND
DROPS 6X

Homeopathic Medicine

Indications

PURPOSE

For temporary relief of sore mouth and gums.

INGREDIENTS

INACTIVE INGREDIENT

10 mL Candida albicans 6X in a base of purified water.

Tamper Evident

Do not use this product if tamper-evident seal on base of bottle cap is missing or broken.

DOSAGE

1-2 × daily 5-10 drops.

WARNING

If symptoms persist more than a few days, contact a licensed practitioner. As with any drug, if you are pregnant or nursing a baby, seek the advice of a health care professional before using this product.

KEEP OUT OF REACH OF CHILDREN

Keep this and all medications out of the reach of children. In case of accidental overdose, seek professional assistance or contact a Poison Control Center immediately.

STORAGE AND HANDLING

Protect from light and heat.

Made in Germany

Distributed by:
SANUM USA Corp.
1465 Slater Road
Ferndale, WA 98248

Manufactured By:
Sanum-Kehlbeck,
GmbH & Co. KG

Rev. 06/2005

PRINCIPAL DISPLAY PANEL - 10 mL Bottle, Dropper Carton

Pleo® San
CAND
DROPS 6X

Homeopathic
Medicine

The original
SANUM®
brand remedies

lndications: For
temporary relief
of sore mouth
and gums.

0.34 fl oz
(10 mL)